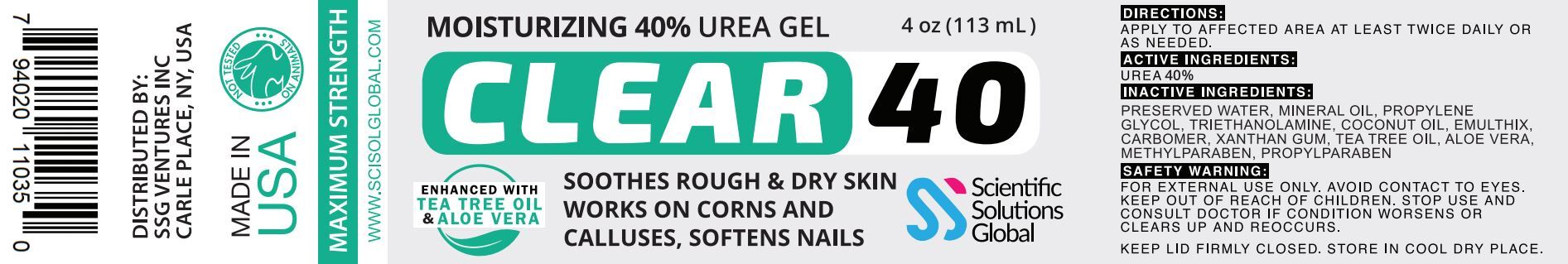 DRUG LABEL: Clear 40
NDC: 81376-231 | Form: GEL
Manufacturer: SSG Ventures Inc
Category: otc | Type: HUMAN OTC DRUG LABEL
Date: 20210210

ACTIVE INGREDIENTS: UREA 40 g/40 g
INACTIVE INGREDIENTS: TRIDECETH-10; XANTHAN GUM; MINERAL OIL; CARBOXYPOLYMETHYLENE; PROPYLENE GLYCOL; ALOE VERA LEAF; COCONUT OIL; WATER; TEA TREE OIL

Clear 40

PACKAGE LABEL

ACTIVE INGREDIENT

Urea 40%

PURPOSE

SOOTHES ROUGH & DRY SKIN

WORKS ON CORNS & CALLUSES

SOFTENS NAILS

INDICATIONS AND USAGE

APPLY TO AFFECTED AREA AT LEAST TWICE DAILY OR AS NEEDED

SAFETY WARNING:

FOR EXTERNAL USE ONLY. AVOID CONTACT TO EYES. KEEP OUT OF REACH OF CHILDREN. STOP USE IF CONDITION WORSENS OR CLEARS UP AND REOCCURS

STORAGE AND HANDLING

KEEP LID FIRMLY CLOSED. STORE IN A COOL DRY PLACE

INACTIVE INGREDIENT

PRESERVED WATER, MINERAL OIL, PROPYLENE GLYCOL, TRIETHANOLAMINE, COCONUT OIL, EMULTHIX, CARBOMER, XANTHAN GUM, TEA TREE OIL, ALOR VERA, METHYLPARABEN, PROPYLPARABEN

DOSAGE AND ADMINISTRATION

APPLY TO AFFECTED AREA AT LEAST TQICE DAILY OR AS NEEDED

WARNINGS

FOR EXTERNAL USE ONLY. AVOID CONTACT TO EYES. KEEP OUT OF REACH OF CHILDREN. STOP USE AND CONSULT A DOCTOR IF CONDITION WORSENS OR CLEARS UP AND REOCCURS

KEEP OUT OF REACH OF CHILDREN

FOR EXTERNAL USE ONLY. AVOID CONTACT TO EYES. KEEP OUT OF REACH OF CHILDREN. STOP USE AND CONSULT A DOCTOR IF CONDITION WORSENS OR CLEARS UP AND REOCCURS